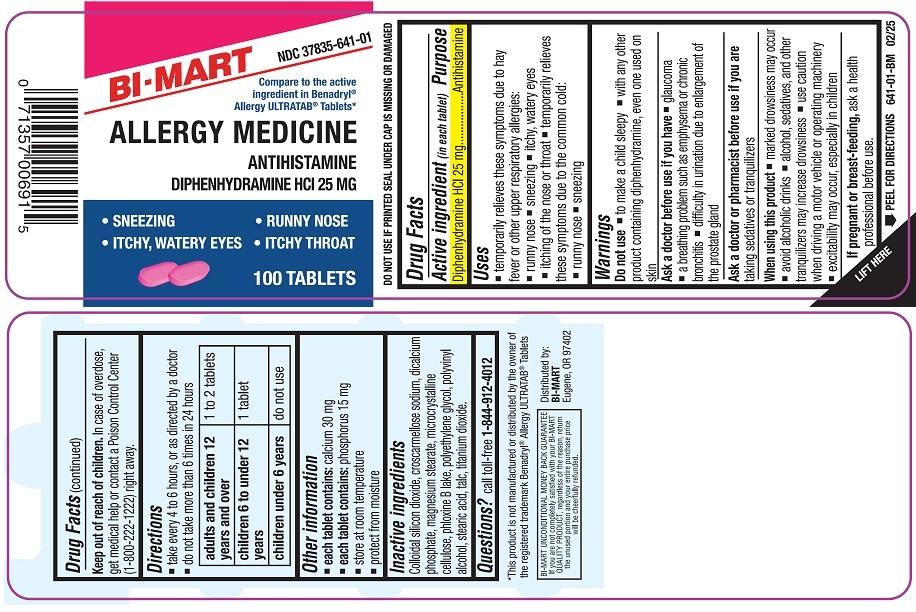 DRUG LABEL: Diphenhydramine Hydrochloride
NDC: 37835-641 | Form: TABLET
Manufacturer: Bi-Mart
Category: otc | Type: HUMAN OTC DRUG LABEL
Date: 20250702

ACTIVE INGREDIENTS: DIPHENHYDRAMINE HYDROCHLORIDE 25 mg/1 1
INACTIVE INGREDIENTS: SILICON DIOXIDE; CROSCARMELLOSE SODIUM; ANHYDROUS DIBASIC CALCIUM PHOSPHATE; MAGNESIUM STEARATE; MICROCRYSTALLINE CELLULOSE; D&C RED NO. 28; POLYETHYLENE GLYCOL, UNSPECIFIED; POLYVINYL ALCOHOL; STEARIC ACID; TALC; TITANIUM DIOXIDE

Active ingredient (in each tablet)

Diphenhydramine HCl 25 mg

Purpose

Antihistamine

Uses

- temporarily relieves these symptoms due to hay fever or other upper respiratory allergies:

o runny nose

o sneezing

o itchy, watery eyes

o itchy of the nose or throat

- temporarily relieves these symptoms of the common cold:

o runny nose
o sneezing

Warnings

Do not use

- to make a child sleepy
- with any other product containing diphenhydramine, even one used on skin

Ask a doctor before use if you have

- glaucoma
- a breathing problem such as emphysema or chronic bronchitis
- difficulty in urination due to enlargement of the prostate gland

Ask a doctor or pharmacist before use if youaretaking sedatives or tranquilizers

When using this product

- marked drowsiness may occur
- avoid alcoholic drinks
- alcohol, sedatives and othe tranquilizers may increase drowsiness
- use caution when driving a motor vehicle or operating machinery
- excitability may occur, especially in children

If pregnant or breast-feeding,

ask a health professional before use

Keep out of reach of children.

In case of overdose, get medical help or contact a Poison Control Center (1-800-222-1222) right away.

Directions

- take every 4 to 6 hours, or as directed by a doctor
- do not take not more than 6 times in 24 hours

- adults and children 12 years and over:1 or 2 tablets
- children 6 to under 12 years:1 tablet
- children under 6 years:do not use

Other Information

- each tablet contains:calcium 30 mg
- each tablet contains:phosphorus 15 mg
- store at room temperature
- protct from moisture
- DO NOT USE IF PRINTED SEAL UNDER CAP IS MISSING OR DAMAGED.

Inactive Ingredients

Colloidal silicon dioxide, croscarmellose sodium, dicalcium phosphate, magnesium stearate, microcrystalline cellulose, phloxine B lake, polyethylene glycol, polyvinyl alcohol, stearic acid, talc, titanium dioxide.

Questions?

call toll free 1-844-912-4012

PRINCIPAL DISPLAY PANEL

NDC 37835-641-01

Compare to the active ingredients in Benadryl®Allergy ULTRATAB®Tablets.*

Allergy Medicine

Antihistamine

Diphenhydramine HCl 25 mg

100 Tablets

*This product is not manufactured or distributed by the owner of the registered trademark Benadryl®Allergy ULTRATAB®Tablets.

Distributed by:

BI-MART

Eugene, OR 97402